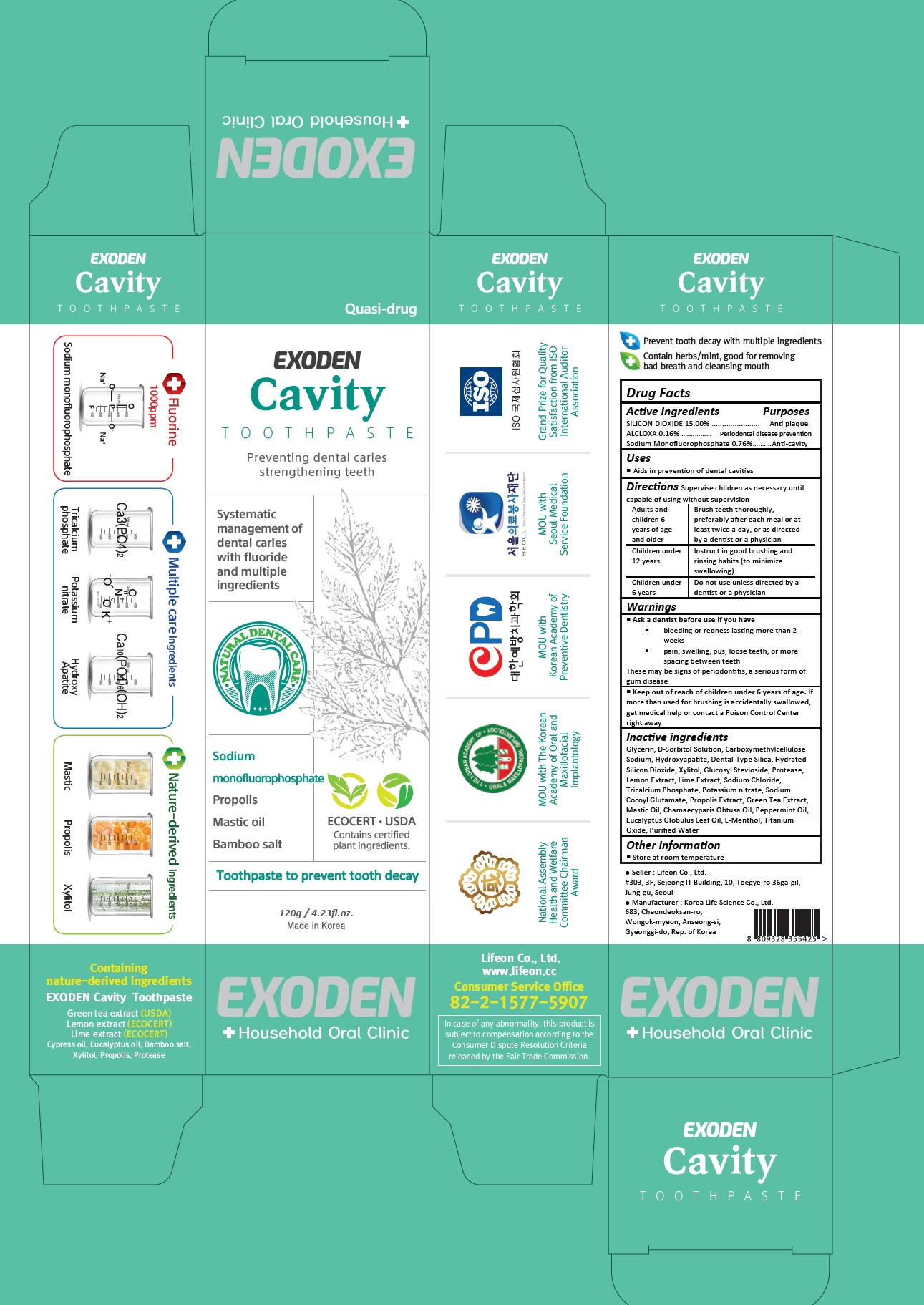 DRUG LABEL: Exoden Cavity
NDC: 70602-005 | Form: PASTE
Manufacturer: LIFEON Corp.
Category: otc | Type: HUMAN OTC DRUG LABEL
Date: 20210310

ACTIVE INGREDIENTS: ALCLOXA 0.16 g/100 g; SILICON DIOXIDE 15 g/100 g; SODIUM MONOFLUOROPHOSPHATE 0.76 g/100 g
INACTIVE INGREDIENTS: GLYCERIN; SORBITOL SOLUTION; CARBOXYMETHYLCELLULOSE SODIUM, UNSPECIFIED; TRIBASIC CALCIUM PHOSPHATE; XYLITOL; GLUCOSYL STEVIOL; LEMON; LIME (CITRUS); SODIUM CHLORIDE; TRICALCIUM PHOSPHATE; POTASSIUM NITRATE; SODIUM COCOYL GLUTAMATE; PROPOLIS WAX; GREEN TEA LEAF; CHAMAECYPARIS OBTUSA WOOD OIL; PEPPERMINT OIL; EUCALYPTUS OIL; LEVOMENTHOL; TITANIUM DIOXIDE; WATER

70602-005_Exoden Cavity Toothpaste

ACTIVE INGREDIENT

Silicon dioxide 15%

Alcloxa 0.16%

Sodium Monofluorophosphate 0.76%

PURPOSE

Anti plaque

Periodontal disease prevention

Anti-cavity

INDICATIONS AND USAGE

Aids in prevention of dental cavities

DOSAGE AND ADMINISTRATION

Supervise children as necessary until capable of using without supervision

Adults and children 6 years of age and older: Brush teeth thoroughly, preferably after each meal or at least twice a day, or as directed by a dentist or a physician

Children under 12 years: Instruct in good brushing and rinsing habits (to minimize swallowing)

Children under 6 years: Do not use unless directed by a dentist or a physician

WARNINGS

Ask a dentist before use if you have
• bleeding or redness lasting more than 2 weeks
• pain, swelling, pus, loose teeth, or more spacing between teeth
These may be signs of periodontitis, a serious form of gum disease

Keep out of reach of children under 6 years of age. If more than used for brushing is accidentally swallowed, get medical help or contact a Poison Control Center right away

INACTIVE INGREDIENT

Glycerin, D-Sorbitol Solution, Carboxymethylcellulose Sodium, Hydroxyapatite, Dental-Type Silica, Hydrated Silicon Dioxide, Xylitol, Glucosyl Stevioside, Protease, Lemon Extract, Lime Extract, Sodium Chloride, Tricalcium Phosphate, Potassium nitrate, Sodium Cocoyl Glutamate, Propolis Extract, Green Tea Extract, Mastic Oil, Chamaecyparis Obtusa Oil, Peppermint Oil, Eucalyptus Globulus Leaf Oil, L-Menthol, Titanium Oxide, Purified Water